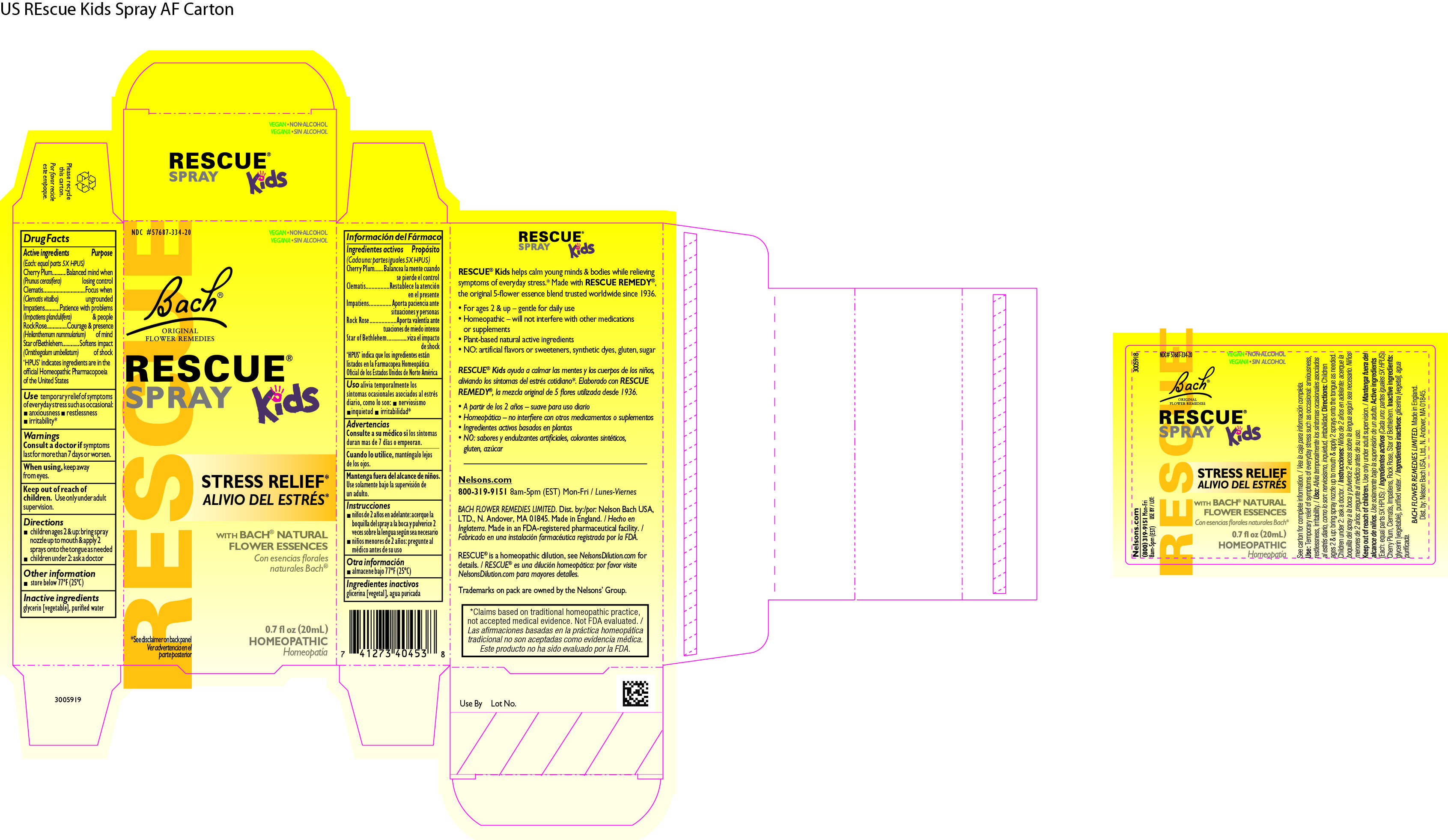 DRUG LABEL: Rescue Remedy Kids
NDC: 57687-334 | Form: SPRAY
Manufacturer: Nelson Bach USA Limited
Category: homeopathic | Type: HUMAN OTC DRUG LABEL
Date: 20240625

ACTIVE INGREDIENTS: CLEMATIS VITALBA FLOWER 5 [hp_X]/0.095 mL; IMPATIENS GLANDULIFERA FLOWER 5 [hp_X]/0.095 mL; HELIANTHEMUM NUMMULARIUM FLOWER 5 [hp_X]/0.095 mL; PRUNUS CERASIFERA FLOWER 5 [hp_X]/0.095 mL; ORNITHOGALUM UMBELLATUM FLOWERING TOP 5 [hp_X]/0.095 mL
INACTIVE INGREDIENTS: WATER; GLYCERIN

Rescue Remedy Kids Spray

Drug Facts - Active Ingredients

Drug Facts

Active ingredients (Each: equal parts 5X HPUS)

Purpose

Cherry Plum (Prunus cerasifera) Balanced mind when losing control

Clematis (Clematis vitalba) Focus when ungrounded

Impatiens (Impatiens glandulifera) Patience with problems& people

Rock Rose (Helianthemum nummularium) Courage & presence of mind

Star of Bethlehem (Ornithogalum umbellatum) Softens impact of shock

‘HPUS’ indicates ingredients are in the official Homeopathic Pharmacopoeia of the United States

Purpose

Use

Use temporary relief of symptoms of everyday stress such as occasional:

anxiousness

restlessness
irritability1

1 Claims based on traditional homeopathic practice, not accepted medical evidence. Not FDA evaluated.

Warnings

Consult a doctor if symptoms last for more than 7 days or worsen.
When using, keep away from eyes.
Keep out of reach of children. Use only under adult supervision.

Directions

children ages 2 & up: bring spray nozzle up to mouth & apply 2 sprays onto the tongue as needed
children under 2: ask a doctor before use

Other information

store below 77ºF (25ºC)

Inactive ingredients

Inactive ingredients glycerin [vegetable], purified water

Questions

(800) 319-9151 Mon-Fri 8am-5pm (EST)

Distributed by

Dist by

Nelson Bach USA,
LTD, N Andover, MA 01845

OTC Purpose

For the relief of occasional stress

Keep out of the reach of children

Primary display panel - Rescue Remedy Kids Spray

Rescue Remedy Kids Spray

NDC 57687-334-20

VEGAN
NON-ALCOHOL

Bach ®
ORIGINAL
FLOWER REMEDIES

RESCUE®
SPRAY KIDS

STRESS
RELIEF*

WITH BACH ®
NATURAL
FLOWER
ESSENCES

0.7 fl oz (20mL)

HOMEOPATHIC

* See disclaimer on
side panel